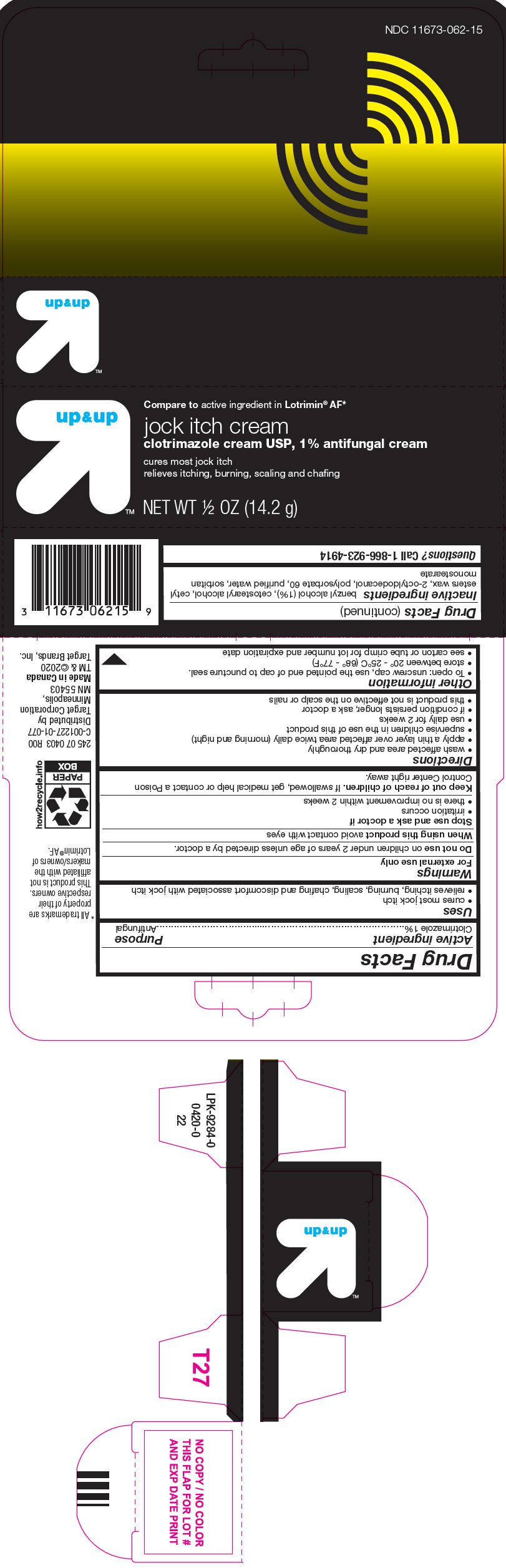 DRUG LABEL: Jock Itch
NDC: 11673-062 | Form: CREAM
Manufacturer: TARGET Corporation
Category: otc | Type: HUMAN OTC DRUG LABEL
Date: 20250716

ACTIVE INGREDIENTS: CLOTRIMAZOLE 10 mg/1 g
INACTIVE INGREDIENTS: BENZYL ALCOHOL; CETOSTEARYL ALCOHOL; CETYL ESTERS WAX; OCTYLDODECANOL; POLYSORBATE 60; WATER; SORBITAN MONOSTEARATE

Jock Itch Cream

Drug Facts

Active ingredient

Clotrimazole 1%

Purpose

Antifungal

Uses

- cures most jock itch
- relieves itching, burning, scaling, chafing and discomfort associated with jock itch

Warnings

For external use only

DO NOT USE

Do not useon children under 2 years of age unless directed by a doctor.

When using this productavoid contact with eyes

Stop use and ask a doctor if

- irritation occurs
- there is no improvement within 2 weeks

Keep out of reach of children.If swallowed, get medical help or contact a Poison Control Center right away.

Directions

- wash affected area and dry thoroughly
- apply a thin layer over affected area twice daily (morning and night)
- supervise children in the use of this product
- use daily for 2 weeks
- if condition persists longer, ask a doctor
- this product is not effective on the scalp or nails

Other information

- To open: unscrew cap, use the pointed end of cap to puncture seal.
- store between 20° - 25°C (68° - 77°F)
- see carton or tube crimp for lot number and expiration date

Inactive ingredients

benzyl alcohol (1%), cetostearyl alcohol, cetyl esters wax, 2-octyldodecanol, polysorbate 60, purified water, sorbitan monostearate

Questions?

Call 1-866-923-4914

Distributed by
Target Corporation
Minneapolis,
MN 55403

PRINCIPAL DISPLAY PANEL - 14.2 g Tube Carton

up & up™

Compare to active ingredient in Lotrimin®AF*

jock itch cream
clotrimazole cream USP, 1% antifungal cream

cures most jock itch
relieves itching, burning, scaling and chafing

NET WT ½ OZ (14.2 g)